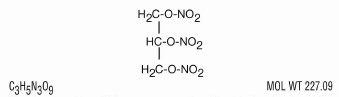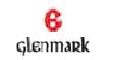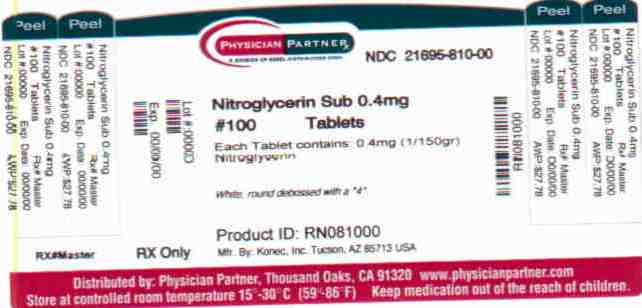 DRUG LABEL: Nitroglycerin
NDC: 21695-810 | Form: TABLET
Manufacturer: Rebel Distributors Corp
Category: prescription | Type: HUMAN PRESCRIPTION DRUG LABEL
Date: 20101008

ACTIVE INGREDIENTS: NITROGLYCERIN 0.4 mg/1 1
INACTIVE INGREDIENTS: LACTOSE; POLYETHYLENE GLYCOL 3350; CELLULOSE, MICROCRYSTALLINE; SILICON DIOXIDE; MAGNESIUM STEARATE

Nitroglycerin Tablets, USP

Rx Only

DESCRIPTION

Nitroglycerin, an organic nitrate, is a vasodilating agent. The chemical name for nitroglycerin is 1,2,3-propanetriol trinitrate. The chemical structure is:

Nitroglycerin tablets USP are compressed sublingual nitroglycerin tablets containing the non-volatile nitroglycerin fixing agent polyethylene glycol. The tablets contain 0.3 mg (1/200 grain), 0.4 mg (1/150 grain), and 0.6 mg (1/100 grain) nitroglycerin. Also contains lactose NF, polyethylene glycol 3350 NF, microcrystalline cellulose NF, colloidal silicon dioxide NF, and magnesium stearate NF.

CLINICAL PHARMACOLOGY

Relaxation of vascular smooth muscle is the principal pharmacologic action of nitroglycerin. The mechanism by which nitroglycerin produces relaxation of smooth muscle is unknown. Although venous effects predominate, nitroglycerin produces, in a dose-related manner, dilation of both arterial and venous beds. Dilation of the postcapillary vessels, including large veins, promotes peripheral pooling of blood and decreases venous return to the heart, reducing left ventricular end-diastolic pressure (preload). Arteriolar relaxation reduces systemic vascular resistance and arterial pressure (afterload). Myocardial oxygen consumption or demand (as measured by the pressure-rate product, tension-time index and stroke-work index) is decreased by both the arterial and venous effects of nitroglycerin, and amore favorable supply-demand ratio can be achieved.

Nitroglycerin also dilates large epicardial coronary arteries; however, the extent to which this effect contributes to the relief of exertional angina is unclear.

Therapeutic doses of nitroglycerin may reduce systolic, diastolic, and mean arterial blood pressure. Effective coronary perfusion pressure is usually maintained, but can be compromised if blood pressure falls excessively or increased heart rate decreases diastolic filling time.

Elevated central venous and pulmonary capillary wedge pressures, pulmonary vascular resistance and systemic vascular resistance are also reduced by nitroglycerin therapy. Heart rate is usually slightly increased, presumably a reflex response to the fall in blood pressure. Cardiac index may be increased, decreased, or unchanged. Patients with elevated left ventricular filling pressure and systemic vascular resistance values in conjunction with a depressed cardiac index are likely to experience an improvement in cardiac index. On the other hand, when filling pressures and cardiac index are normal, cardiac index may be slightly reduced by intravenous nitroglycerin.

Mechanism of Action

Nitroglycerin forms free radical nitric oxide (NO) which activates guanylate cyclase, resulting in an increase of guanosine 3'5' monophosphate (cyclic GMP) in smooth muscle and other tissues. This eventually leads to dephosphorylation of the light chain of myosin, which regulates the contractile state in smooth muscle, resulting in vasodilation.

Pharmacokinetics and Metabolism

Nitroglycerin is rapidly absorbed following sublingual administration. Its onset of action is approximately one to three minutes. Significant pharmacologic effects are present for 30 to 60 minutes following administration by the above route.

Nitroglycerin is rapidly metabolized to dinitrates and mononitrates, with a short half-life, estimated at 1 to 4 minutes. A liver reductase enzyme is of primary importance in the metabolism of nitroglycerin to glycerol nitrate metabolites and organic nitrate. Two active major metabolites 1,2- and 1,3-dinitroglycerols are less potent vasodilators and have longer half-lives than the parent compound. Dinitrates are metabolized to mononitrates and ultimately glycerol. The monohydrate is not considered biologically active with respect to cardiovascular effects.

At plasma concentrations of between 50 and 500 ng/mL, the binding of nitroglycerin to plasma proteins is approximately 60%, while that of 1,2dinitroglycerin and 1,3-dinitroglycerin is 60% and 30%, respectively. The activity and half-life of 1,2-dinitroglycerin and 1,3-dinitroglycerin are not well characterized. The mononitrate is not active.

INDICATIONS AND USAGE

Nitroglycerin is indicated for the acute relief of an attack or prophylaxis of angina pectoris due to coronary artery disease.

CONTRAINDICATIONS

Sublingual nitroglycerin therapy is contraindicated in patients with early myocardial infarction, severe anemia, increased intracranial pressure and those with a known hypersensitivity to nitroglycerin.

Administration of Nitroglycerin tablets USP is contraindicated in patients who are using Viagra® (sildenafil citrate). Viagra® has been shown to potentiate the hypotensive effects of organic nitrates.

WARNINGS

The use of nitroglycerin during the early course of acute myocardial infarction requires particular attention to hemodynamic monitoring and clinical status.

PRECAUTIONS

General

Only the smallest dose required for effective relief of the acute anginal attack should be used. Excessive use may lead to the development of tolerance. Nitroglycerin USP tablets are intended for sublingual or buccal administration and should not be swallowed. Severe hypotension, particularly with upright posture, may occur even with small doses of nitroglycerin. The drug should be used cautiously in patients with volume depletion or low systolic blood pressure.

Paradoxical bradycardia and increased angina pectoris may accompany nitroglycerin-induced hypotension.

Nitrate therapy may aggravate angina caused by hypertrophic cardiomyopathy.

Tolerance to the vascular and antianginal effects of nitroglycerin and cross-tolerance to other nitrates and nitrites may occur.

The drug should be discontinued if blurring of vision or drying of the mouth occurs. Excessive dosage of nitroglycerin may produce severe headaches.

Information for patients

If possible, patients should sit down when taking Nitroglycerin tablets USP. This eliminates the possibility of falling due to lightheadedness or dizziness.

Nitroglycerin may produce a burning or tingling sensation when administered sublingually; however, the ability to produce a burning or tingling sensation should not be considered a reliable method for determining the potency of the tablets.

Nitroglycerin should be kept in the original glass container, tightly capped. The cotton should be discarded once the bottle is opened.

Administration of Nitroglycerin tablets USP is contraindicated in patients who are using Viagra® (sildenafil citrate). Viagra® has been shown to potentiate the hypotensive effects of organic nitrates (see CONTRAINDICATIONS).

Interactions

Drug interactions

Concomitant use of nitrates and alcohol may cause hypotension. Patients receiving antihypertensive drugs, beta-adrenergic blockers or phenothiazines and nitrates should be observed for possible additive hypotensive effects. Marked orthostatic hypotension has been reported when calcium channel blockers and organic nitrates were used concomitantly. Dose adjustment of either class of agent may be necessary.

Aspirin may decrease the clearance and enhance the hemodynamic effects of sublingual nitroglycerin. A decrease in the therapeutic effect of sublingual nitroglycerin may result from use of long-acting nitrates.

Drug/laboratory test interactions

Nitrates may interfere with the Ziatkis-Zak color reaction causing a false report of decreased serum cholesterol.

Carcinogenesis, mutagenesis, impairment of fertility

No long-term studies in animals were performed to evaluate the carcinogenic potential of nitroglycerin.

Pregnancy

Pregnancy Category C

Animal reproduction studies have not been conducted with nitroglycerin. It is also not known whether nitroglycerin can cause fetal harm when administered to a pregnant woman or can affect reproduction capacity. Nitroglycerin should be given to apregnant woman only if clearly needed.

Nursing mothers

It is not known whether nitroglycerin is excreted in human milk. Because many drugs are excreted in human milk, caution should be exercised when intravenous nitroglycerin is administered to a nursing woman.

Pediatric use

The safety and effectiveness of nitroglycerin in pediatric patients have not been established.

ADVERSE REACTIONS

Headache which may be severe and persistent may occur immediately after use. Vertigo, weakness, palpitation and other manifestations of postural hypotension may develop occasionally, particularly in erect, immobile patients. Marked sensitivity to the hypotensive effects of nitrates (manifested by nausea, vomiting, weakness, diaphoresis, pallor and collapse) may occur at therapeutic doses. Syncope due to nitrate vasodilation has been reported. Flushing, drug rash, and exfoliative dermatitis have been reported in patients receiving nitrate therapy.

OVERDOSAGE

Nitrate overdose may result in: severe hypotension, tachycardia, bradycardia, heart block, palpitation, death due to circulatory collapse, syncope, persistent throbbing headache, vertigo, visual disturbance, increased intracranial pressure, paralysis, and coma followed by convulsions, flushing and diaphoresis, nausea and vomiting, colic and diarrhea, dyspnea, methemoglobinemia.

Since hypotension from nitroglycerin overdosage results from venodilation and arterial hypovolemia, therapy should be directed toward central volume expansion. Elevation of extremities may be sufficient, but intravenous infusion may also be necessary. Use of arterial vasoconstrictors may do more harm than good. Management of nitroglycerin overdose in patients with renal disease or congestive heart failure may require invasive monitoring.

If methemoglobinemia is present, intravenous administration of methylene blue 1-2 mg/kg of body weight may be required.

DOSAGE AND ADMINISTRATION

One tablet should be dissolved under the tongue or in the buccal pouch at the first sign of an acute anginal attack. The dose may be repeated approximately every five minutes, until relief is obtained. If the pain persists after a total of 3 tablets in a 15-minute period, prompt medical attention is recommended. Nitroglycerin tablets USP may be used prophylactically 5 to 10 minutes prior to engaging in activities which might precipitate an acute attack.

During administration the patient should rest, preferably in the sitting position.

No dosage adjustment is required in patients with renal failure.

HOW SUPPLIED

Nitroglycerin Tablets, USP are supplied as follows:

0.4 mg - White tablet embossed with a "4".
4 x Bottles of 25: NDC 21695-697-25
Bottle of 100: NDC 21695-810-00

STORAGE AND HANDLING

Store up to 25o C (77o F). Protect from moisture.

Manufactured By:

Konec, Inc,
Tucson, AZ 65713

Manufactured For:

Glenmark Generics Inc., USA
Mahwah, NJ 07430

Questions? 1 (888) 721-7115
www.glenmarkgenerics.com

Repackaged by:

Rebel Distributors Corp

Thousand Oaks, CA 91320

NITROGLYCERIN TABLETS USP Patient Information Booklet

This booklet provides general guidance and instruction on the use of Nitroglycerin Tablet USP. You should use this booklet as a handy reminder of your doctor's instructions. Remember to always follow the directions your doctor gave you, and ask your doctor if you have any questions about Nitroglycerin Tablets therapy.

Nitroglycerin Tablets should not be used if you are severely anemic, have been diagnosed with increased pressure on the brain, or are sensitive/allergic to Nitroglycerin. If you are taking Nitroglycerin Tablets, you should not take Viagra® (sildenafil citrate).

While using Nitroglycerin Tablets, if you experience blurring of vision or drying of the mouth, discontinue use and let your doctor know. Nitroglycerin Tablets may cause anotable drop in blood pressure if you are taking blood pressure medication, consuming alcohol, or taking nitrates or antipsychotics.

Excessive use of Nitroglycerin Tablets may lead to tolerance. Headache may occur immediately after Nitroglycerin Tablets use. Dizziness, weakness, and fainting may develop occasionally, especially in patients who are not lying down. The cancer-causing potential of Nitroglycerin Tablets is unknown. Unless specifically prescribed by a physician, Nitroglycerin Tablets should not be used in pregnant or nursing women or in children.

What is angina?

Angina is a medical condition that causes you to feel temporary pain in your chest. The pain may range from adull ache to a severe, crushing sensation. Attacks can occur several times a day or every few weeks, months, or years.

What causes angina?

Angina occurs when your heart muscle needs more oxygen than it can get. This can happen at almost any time, especially during or following physical exertion, stress, or exposure to cold air.

What happens if angina is not treated?

Angina is serious, and, if left untreated, it can lead to additional medical problems such as heart attack. Your angina therapy could save your life. Please read this booklet and make sure to follow your doctor's directions for your angina therapy. Be sure to carry your Nitroglycerin Tablets with you at all times because you never know when you will need them.

How is angina treated?

In addition to having patients modify their activities, one of the most commonly prescribed medications for angina is nitroglycerin. Nitroglycerin Tablets USP and the nitroglycerin patches are nitrates, a form of nitroglycerin. Nitroglycerin Tablets can be used immediately prior to activities that may bring on an angina attack and to treat an angina attack that has already started.

What are Nitroglycerin Tablets USP and how do they work?

Nitroglycerin Tablets USP are a form of nitroglycerin used to relieve or prevent episodes of acute angina. The drug is taken sublingually, meaning it is placed under the tongue to dissolve. Nitroglycerin Tablets can relieve angina by dilating the arteries of the heart so that more oxygen-carrying blood can reach the heart muscle.

How should I use Nitroglycerin Tablets USP when I am having an angina attack?

You may use up to three Nitroglycerin Tablets USP in a 15 minute period. If you continue to feel pain after 15 minutes, call your doctor or seek medical attention immediately. Stay calm and be aware that this unrelieved pain does not necessarily mean you are having a heart attack.

Always follow your doctors directions for use. In general, the following schedule should be followed:

ONSET:

At the first sign of an attack, sit down and then place one Nitroglycerin Tablet under your tongue. You should take Nitroglycerin Tablets while sitting because your blood pressure may drop and cause lightheadedness and dizziness.

5 MIN:

If after waiting 5 minutes, your pain is still present, take a second Nitroglycerin Tablet.

10 MIN:

Again, if after waiting another 5 minutes, the pain is still present, you should take a third Nitroglycerin Tablet.

15 MIN:

If the pain continues 5 minutes or longer after your third Nitroglycerin Tablet, call your doctor or seek medical attention immediately to find out what to do next.

Can I use Nitroglycerin Tablets USP to prevent an angina attack?

Nitroglycerin Tablets may also be used immediately before activities that you feel might cause an angina attack, such as exercise or sexual intercourse. Since you are the best judge of what may set off an attack, be sure to have a bottle of Nitroglycerin Tablets on hand for those times in those places where you would most expect an attack. Take one Nitroglycerin Tablet 5 to 10 minutes before you begin these activities, or follow your doctor's recommendations.

Can I swallow Nitroglycerin Tablets USP?

No. It is very important that each Nitroglycerin Tablet be placed under the tongue until it has fully dissolved. Nitroglycerin Tablets should not be chewed, crushed or swallowed.

Can I eat, drink, or smoke while using Nitroglycerin Tablets USP?

No, do not eat, drink any beverages (including alcohol), smoke, or use chewing tobacco while a tablet is dissolving and/or when you are experiencing acute chest pain.

Should I expect any side effects when I take Nitroglycerin Tablets USP?

Some patients may feel a slight stinging sensation while the tablet is dissolving under the tongue. You also might experience warmth and flushing of the face or lightheadedness and dizziness. Sometimes, patients experience mild to severe headaches with their first few Nitroglycerin Tablets. These side effects usually are not signs of other problems, but you should let your doctor know if you have any concerns.

Why does this package contain four bottles of Nitroglycerin Tablets USP?

Instead of one bottle of 100 tablets, each bottle of Nitroglycerin Tablets USP in the 4-by-25 pack contains 25 tablets. Therefore, you can place the bottles in locations where you might have an angina attack, such as your bedroom, workroom, kitchen, or office. Also, you should always keep a bottle in a jacket or coat pocket (not a shirt or trouser pocket) or purse. By keeping Nitroglycerin Tablets in multiple locations, you will be sure to have your Nitroglycerin Tablets nearby when you need it.

What are the advantages of the 4-by-25 pack?

When purchasing just one 100-tablet bottle, patients cannot keep the drug in different locations without removing tablets from the original container. This is a problem since only the original containers protect Nitroglycerin Tablets from air, heat, moisture, and light. Exposure to these elements can reduce the strength of Nitroglycerin Tablets. Use of the 4-by-25 pack is a convenient way to properly store Nitroglycerin Tablets.

Why isn't there cotton in the Nitroglycerin Tablets USP?

The cotton has been left out of these bottles to make it as easy as possible for you to get a tablet when you need one.

How should I store Nitroglycerin Tablets USP?

Keep bottles where you are likely to have an angina attack, and remember to always keep one bottle with you - for example, in a pocketbook, tote bag, or overcoat. Keep the bottle loose and away from your body to protect the medication from body heat. Nitroglycerin Tablets bottles should not be kept in trouser or shirt pockets. To protect against loss of potency, Nitroglycerin Tablets should be stored in the original bottle and the bottle kept tightly closed. Nitroglycerin Tablets should not be placed in a pillbox or any other container. Do not place other medication in the Nitroglycerin Tablets bottle. Do not refrigerate Nitroglycerin Tablets; room temperature is best. As with all medications, keep Nitroglycerin Tablets out of the reach of children.

How do I know when to replace a bottle of Nitroglycerin Tablets USP?

If the medication has been exposed to ahigh temperature or if the date on the bottle has expired, it should be discarded. Your pharmacist can help determine if your Nitroglycerin Tablets should be replaced.

Manufactured By:

Konec, Inc,
Tucson, AZ 65713

Manufactured For:

Glenmark Generics Inc., USA
Mahwah, NJ 07430

Questions? 1 (888) 721-7115
www.glenmarkgenerics.com

Repackaged by:

Rebel Distributors Corp

Thousand Oaks, CA 91320